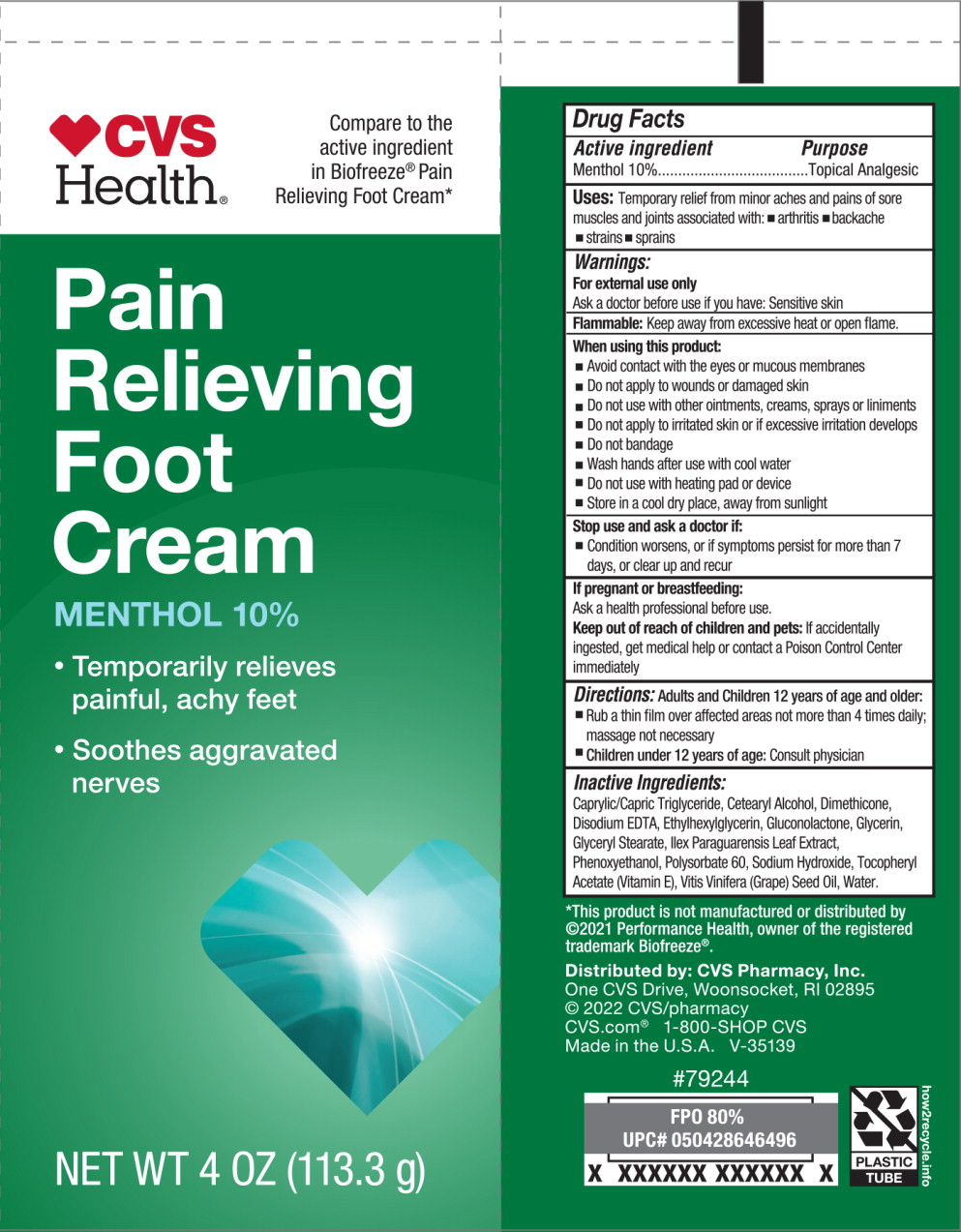 DRUG LABEL: CVS Health Pain Relief Foot
NDC: 66902-292 | Form: CREAM
Manufacturer: NATURAL ESSENTIALS, INC.
Category: otc | Type: HUMAN OTC DRUG LABEL
Date: 20241004

ACTIVE INGREDIENTS: MENTHOL, UNSPECIFIED FORM 100 mg/1 g
INACTIVE INGREDIENTS: MEDIUM-CHAIN TRIGLYCERIDES; CETOSTEARYL ALCOHOL; DIMETHICONE; EDETATE DISODIUM; ETHYLHEXYLGLYCERIN; GLUCONOLACTONE; GLYCERIN; GLYCERYL MONOSTEARATE; ILEX PARAGUARIENSIS LEAF; PHENOXYETHANOL; POLYSORBATE 60; SODIUM HYDROXIDE; .ALPHA.-TOCOPHEROL ACETATE; GRAPE SEED OIL; WATER

Drug Facts

Active ingredient

Menthol 10%

Purpose

Topical Analgesic

Uses:

Temporary relief from minor aches and pains of sore muscles and joints associated with:

- arthritis
- backache
- strains
- sprains

Warnings:

For external use only

Ask a doctor before use if you have: Sensitive skin

Flammable:Keep away from excessive heat or open flame.

When using this product:

- Avoid contact with the eyes or mucous membranes
- Do not apply to wounds or damaged skin
- Do not use with other ointments, creams, sprays or liniments
- Do not apply to irritated skin or if excessive irritation develops
- Do not bandage
- Wash hands after use with cool water
- Do not use with heating pad or device
- Store in a cool dry place, away from sunlight

Stop use and ask a doctor if:

- Condition worsens, or if symptoms persist for more than 7 days, or clear up and recur

If pregnant or breastfeeding:

Ask a health professional before use.

Keep out of reach of children and pets:If accidentally ingested, get medical help or contact a Poison Control Center immediately

Directions:

Adults and Children 12 years of age and older:

- Rub a thin film over affected areas not more than 4 times daily; massage not necessary
- Children under 12 years of age: Consult physician

Inactive Ingredients:

Caprylic/Capric Triglyceride, Cetearyl Alcohol, Dimethicone, Disodium EDTA, Ethylhexylglycerin, Gluconolactone, Glycerin, Glyceryl Stearate, Ilex Paraguarensis Leaf Extract, Phenoxyethanol, Polysorbate 60, Sodium Hydroxide, Tocopheryl Acetate (Vitamin E), Vitis Vinifera (Grape) Seed Oil, Water.

Principal Display Panel – 113.3 g Tube Label

cvs
Health ®

Compare to the active ingredient in Biofreeze®Pain Relieving Foot Cream*

Pain Relieving Foot Cream

MENTHOL 10%

- Temporarily relieves painful, achy feet
- Soothes aggravated nerves

NET WT 4 OZ (113.3 g)